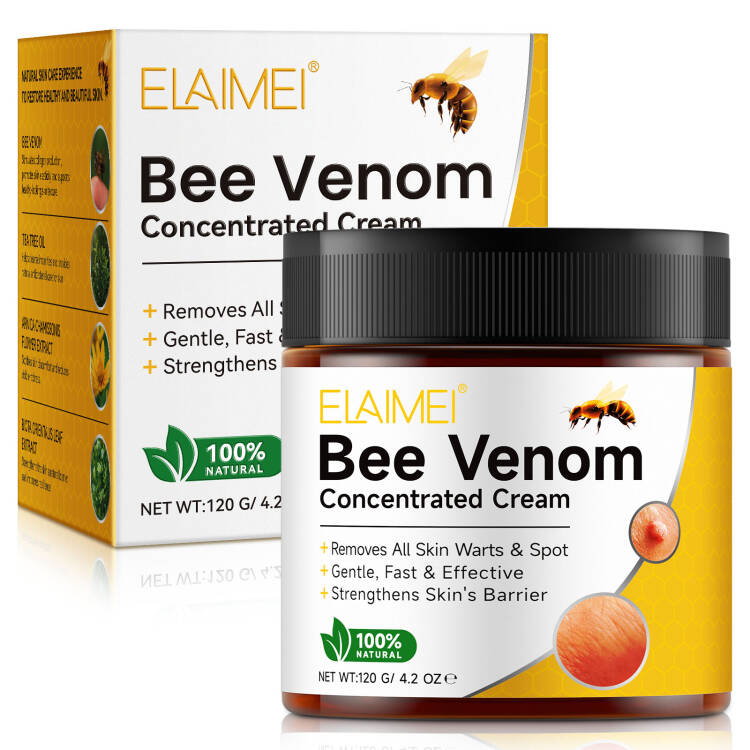 DRUG LABEL: ELAIMEI Bee Venom Concentrated Cream
NDC: 83804-014 | Form: CREAM
Manufacturer: Shenzhen Shandian Jingling Technology Co., Ltd.
Category: otc | Type: HUMAN OTC DRUG LABEL
Date: 20260127

ACTIVE INGREDIENTS: APIS MELLIFERA VENOM 5 g/100 g
INACTIVE INGREDIENTS: WATER; MELALEUCA ALTERNIFOLIA (TEA TREE) LEAF OIL; ARNICA CHAMISSONIS FLOWER; PLATYCLADUS ORIENTALIS LEAF

83804-014 ELAIMEI Bee Venom Concentrated Cream

ACTIVE INGREDIENT

Bee Venom

PURPOSE

skincare

INDICATIONS AND USAGE

NATURAL SKIN CARE EXPERIENCETO RESTORE HEALTHY AND BEAUTIFUL SKIN.

WARNINGS

Forexternal use only.

Do not apply todamaged skin.
Not suitable for use by children, pregnant women,or lactating individuals.

STOP USE

lf irritation occurs,discontinue use immediately and consult a healthcareprofessional.

WHEN USING

For external use only. Individual results may vary. This productmay cause allergies in some individuals.

Keep out of reach of children.

DOSAGE AND ADMINISTRATION

1. Begin by thoroughly cleansing the skin area.
2. Apply evenly a small amount of cream directly to the mole orwart.
3. Massage gently in circular motions with your hands until fullyabsorbed.

INACTIVE INGREDIENT

Aqua (Water)

Arnica Chamissonis Flower Extract
Melaleuca Alternifolia (Tea Tree) Leaf Oil
Biota Orientalis Leaf Extract